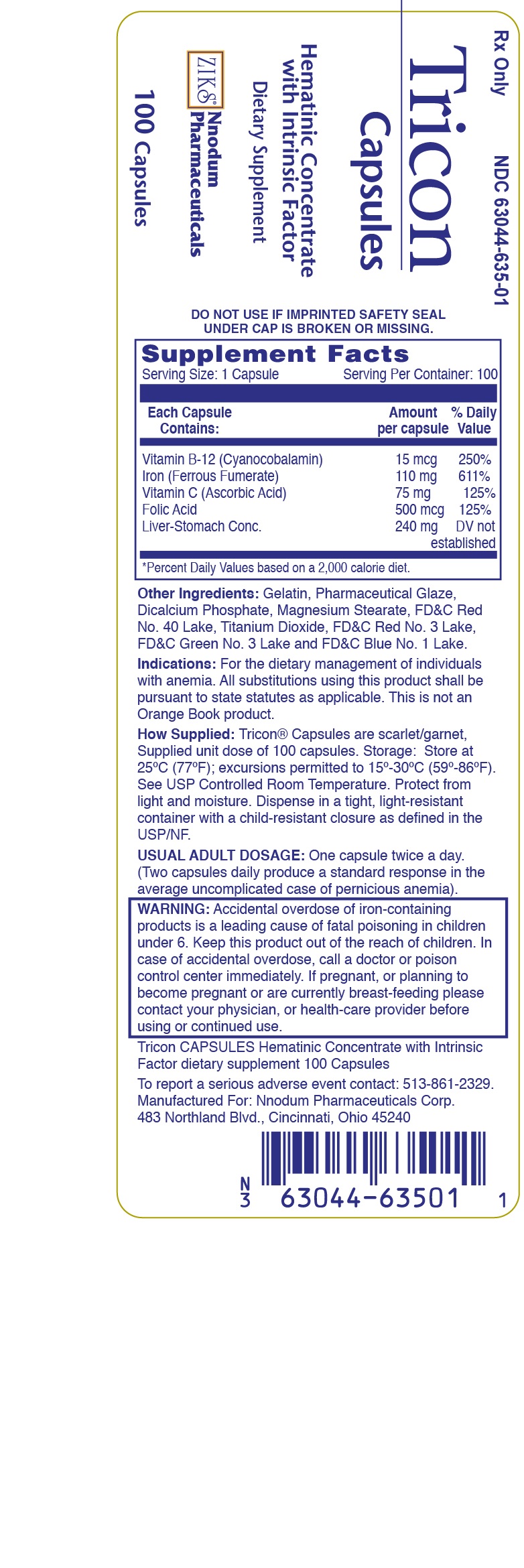 DRUG LABEL: TRICON
NDC: 63044-635 | Form: CAPSULE
Manufacturer: Nnodum Pharmaceuticals
Category: prescription | Type: HUMAN PRESCRIPTION DRUG LABEL
Date: 20251229

ACTIVE INGREDIENTS: CYANOCOBALAMIN 15 ug/1 1; FERROUS FUMARATE 110 mg/1 1; ASCORBIC ACID 75 mg/1 1; FOLIC ACID 0.5 mg/1 1
INACTIVE INGREDIENTS: CITRIC ACID MONOHYDRATE; D&C YELLOW NO. 10; ETHYLCELLULOSE, UNSPECIFIED; FD&C BLUE NO. 1; GELATIN; LECITHIN, SOYBEAN; MAGNESIUM STEARATE; SILICON DIOXIDE; SODIUM BENZOATE; SODIUM CITRATE; SORBIC ACID; STARCH, CORN; TITANIUM DIOXIDE

TRICON™ Capsules

Liver Stomach Concentrate Capsule

Hematinic Conentrate with Intrinsic Factor

NDC 63044-635-10

Rx Only

WARNING: Accidental overdose of iron containing products is a leading cause of fatal poisoning in children under 6. Keep this product out of reach of children. In case of accidental overdose, call a doctor or poison control center immediately.

A Highly Potent Oral Antianemia Preparation

DESCRIPTION

Each TRICON™ Capsule contains:

Special liver-stomach concentrate

(containing intrinsic factor). . . . . . . . . . . . . . . . 240 mg

Vitamin B12 (activity equivalent) . . . . . . . . . . . .15 mcg

Iron, elemental (ferrous fumarate) . . . . . . . . . .110 mg

Vitamin C (ascorbic acid) . . . . . . . . . . . . . . . . . 75 mg

Folic acid . . . . . . . . . . . . . . . . . . . . . . . . . . . . 0.5 mg

with other factors of vitamin B complex present in the liver-stomach concentrate.

Inactive ingredients: Citric acid, D&C Yellow No. 10, ethylcellulose, FD&C Blue No. 1, FD&C Red #28, gelatin, lecithin, magnesium stearate, pharmaceutical glaze, silicon dioxide, simethicone, sodium benzoate, sodium citrate, sorbic acid, starch, and titanium dioxide.

CLINICAL PHARMACOLOGY: Vitamin B12 with Intrinsic

Factor: when secretion of intrinsic factor in gastric juice is inadequate or absent (e.g., Addisonian pernicious anemia or after gastrectomy), vitamin B12 in physiologic doses is absorbed poorly, if at all. The resulting deficiency of vitamin B12 leads to the clinical manifestations of pernicious anemia. Similar megaloblastic anemias may develop in fish tapeworm (Diphyllobothrium latum) infection or after a surgically created small bowel blind loop; in these situations, treatment requires freeing the host of the parasites or bacteria that appear to compete for the available vitamin B12. Strict vegetarianism and malabsorption syndromes may also lead to vitamin B12 deficiency. In the latter case, parenteral therapy or oral therapy with so-called massive doses of vitamin B12 may be necessary for adequate treatment of the patient.

Potency of intrinsic factor concentrates is determined physiologically, i.e., by their use in patients with pernicious anemia. The liver-stomach concetrate with intrinsic factor and the vitamin B12 contained in two TRICON™ Capsules provide 1½ times the minimum amount of therapeutic agent that, when given daily in an uncomplicated case of pernicious anemia, will produce a satisfactory response and relief of anemia and symptoms.

Concentrates of intrinsic factor derived from hog gastric, pyloric, and duodenal mucosa have been used successfully in patients who lack intrinsic factor.

Folic Acid: Folic acid deficiency is the immediate cause of most, if not all, cases of nutritional megaloblastic anemia and of the megaloblastic anemias of pregnancy and infancy; usually, it is also at least partially responsible for the megaloblastic anemias of malabsorption syndromes, e.g., tropical and nontropical sprue.

It is apparent that in vitamin B12 deficiency (e.g., pernicious anemia) lack of this vitamin results in impaired utilization of folic acid. There are other evidences of the close folic acid-vitamin B12 interrelationship: (1) B12 influences the storage, absorption, and utilization of folic acid, and (2) as a deficiency of B12 progresses, the requirement for folic acid increases. However, folic acid does not change the requirements for vitamin B12.

Iron: A very common anemia is that due to iron deficiency. In most cases, the response to iron salts is prompt, safe, and predictable. Within limits, the response is quicker and more certain to large doses of iron than to small doses.

Each TRICON™ (hematinic concentrate with intrinsic factor) Capsule furnishes 110 mg of elemental iron (as ferrous fumarate) to provide a maximum response.

Ascorbic Acid: Vitamin C plays a role in anemia therapy. It augments the conversion of folic acid to its active form, folinic acid. In addition, ascorbic acid promotes the reduction of ferric iron in food to the more readily absorbed ferrous form. Severe and prolonged vitamin C deficiency is associated with an anemia that is usually hypochromic but occasionally megaloblastic in type.

INDICATIONS AND USAGE

TRICON™ is a multifactor preparation effective in the treatment of anemias that respond to oral hematinics, including pernicious anemia and other megaloblastic anemias and also irondeficiency anemia. Therapeutic quantities of hematopoietic factors that are known to be important are present in the recommended daily dose.

CONTRAINDICATIONS

Hemochromatosis and hemosiderosis are contraindications to iron therapy.

PRECAUTIONS

General

Anemia is a manifestation that requires appropriate investigation to determine its cause or causes.

Folic acid alone is unwarranted in the treatment of pure vitamin B12 deficiency states, such as pernicious anemia. Folic acid may obscure pernicious anemia in that the blood picture may revert to normal while neurological manifestations remain progressive.

As with all preparations containing intrinsic factor, resistance may develop in some cases of pernicious anemia to the potentiation of absorption of physiologic doses of vitamin B12. If resistance occurs, parenteral therapy or oral therapy with so-called massive doses of vitamin B12 may be necessary for adequate treatment of the patient. No single regimen fits all cases, and the status of the patient observed in follow-up is the final criterion for adequacy of therapy. Periodic clinical and laboratory studies are considered essential and are recommended.

Pregnancy

Teratogenic Effects

Pregnancy Category C:

Animal reproduction studies have not been conducted with TRICON™ Capsules. It is also not known whether TRICON™ Capsules can cause fetal harm when administered to pregnant women or can affect reproduction capacity. TRICON™ Capsules should be given to pregnant women only if clearly needed.

Nursing Mothers

It is not known whether this drug is excreted in human milk. Because many drugs are excreted in human milk, caution should be exercised when TRICON™ is administered to a nursing woman.

Pediatric Use

Safety and effectiveness in pediatric patients below the age of 10 have not been established.

Geriatric Use

Geriatric Use: Clinical studies on this product have not been performed in sufficient numbers of subjects aged 65 and over to determine whether elderly subjects respond differently from younger subjects. In general, dose selection for an elderly patient should be cautious, usually starting at the low end of the dosing range, reflecting the greater frequency of decreased hepatic, renal or cardiac function and of concomitant disease or other drug therapy.

ADVERSE REACTIONS

Rarely, iron in therapeutic doses produces gastrointestinal reactions, such as diarrhea or constipation. Reducing the dose and administering it with meals will minimize these effects in the iron-sensitive patient.

In extremely rare instances, skin rash suggesting allergy has been noted following the oral administration of liver-stomach material. Allergic sensitization has been reported following both oral and parenteral administration of folic acid.

OVERDOSAGE

Symptoms: Those of iron intoxication, which may include pallor and cyanosis, vomiting, hematemesis, diarrhea, melena, shock, drowsiness, and coma.

Treatment: For specific therapy, exchange transfusion and chelating agents. For general management, gastric and rectal lavage with sodium bicarbonate solution or milk, administration of intravenous fluids and electrolytes, and use of oxygen.

DOSAGE AND ADMINISTRATION

One capsule twice a day. (Two capsules daily produce a standard response in the average uncomplicated case of pernicious anemia.)

HOW SUPPLIED

TRICON™ Capsules are opaque brown NDC 63044-0635-10 Unit Dose Packs containing 10 capsules per card. 100 capsules.

Storage: Store at controlled room temperature 25°C (77°F); excursions permitted to 15°-30°C (59°-86°F). [See USP Controlled Room Temperature.

Manufactured For
Nnodum Pharmaceuticals by Contract Pharmacal Corporation
135 Adams Avenue
Hauppauge, New York 11788

PACKAGE LABEL.PRINCIPAL DISPLAY PANEL

Rx Only NDC 63044-635-01

Tricon

Capsules

100 Capsules

Manufactured for Nnodum Pharmaceuticals Corp.

483 Northland Blvd., Cincinnati, OH 45240

res